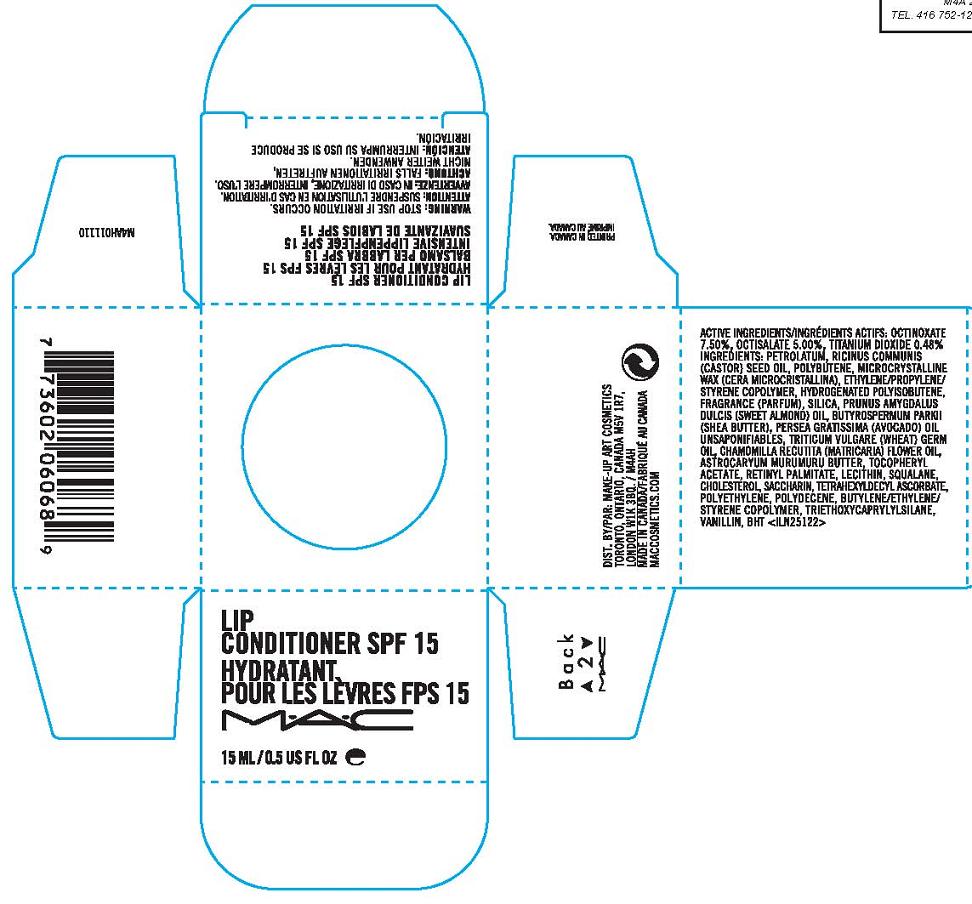 DRUG LABEL: TINTED LIP CONDITIONER
NDC: 40046-0049 | Form: GEL
Manufacturer: MAKEUP ART COSMETICS
Category: otc | Type: HUMAN OTC DRUG LABEL
Date: 20110912

ACTIVE INGREDIENTS: OCTINOXATE 7.5 mL/100 mL; OCTISALATE 5.0 mL/100 mL
INACTIVE INGREDIENTS: PETROLATUM; CASTOR OIL; MICROCRYSTALLINE WAX; SILICON DIOXIDE               ; POLYISOBUTYLENE (35000 MW); LECITHIN, SOYBEAN; ALMOND OIL; SHEA BUTTER; ASTROCARYUM MURUMURU SEED BUTTER; CHOLESTEROL; WHEAT GERM OIL; HIGH DENSITY POLYETHYLENE; TRIETHOXYCAPRYLYLSILANE; STANNIC OXIDE                    ; SACCHARIN; BUTYLATED HYDROXYTOLUENE

ACTIVE INGREDIENTS: OCTINOXATE 7.50% [] OCTISALATE 5.00%

INACTIVE INGREDIENT

INACTIVE INGREDIENTS: PETROLATUM [] RICINUS COMMUNIS (CASTOR) SEED OIL [] POLYBUTENE [] MICROCRYSTALLINE WAX \CERA MICROCRISTALLINA\CIRE MICROCRISTALLINE [] ETHYLENE/PROPYLENE/STYRENE COPOLYMER [] HYDROGENATED POLYISOBUTENE [] FRAGRANCE (PARFUM) [] SILICA [] BUTYROSPERMUM PARKII (SHEA BUTTER) [] PERSEA GRATISSIMA (AVOCADO) OIL UNSAPONIFIABLES [] TRITICUM VULGARE (WHEAT) GERM OIL [] CHAMOMILLA RECUTITA (MATRICARIA) FLOWER OIL [] ASTROCARYUM MURUMURU BUTTER [] PRUNUS AMYGDALUS DULCIS (SWEET ALMOND) OIL [] TOCOPHERYL ACETATE [] RETINYL PALMITATE [] CHOLESTEROL [] LECITHIN [] SQUALANE [] POLYETHYLENE [] POLYDECENE [] BUTYLENE/ETHYLENE/STYRENE COPOLYMER [] TRIETHOXYCAPRYLYLSILANE [] TETRAHEXYLDECYL ASCORBATE [] SACCHARIN [] VANILLIN [] BHT

WARNINGS

WARNING: STOP USE IF IRRITATION OCCURS.

PACKAGE LABEL

PRINCIPAL DISPLAY PANEL:

MAC

LIP CONDITIONER SPF 15

15 ML/0.5 US FL OZ.

DISTR. BY MAKEUP ART COSMETICS
TORONTO, ONTARIO, CANADA, M5V 1R7